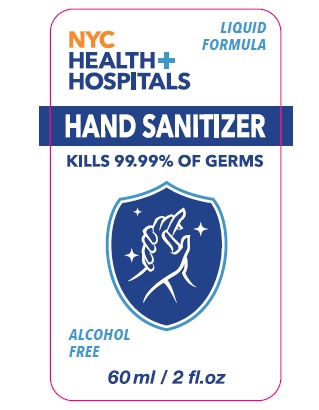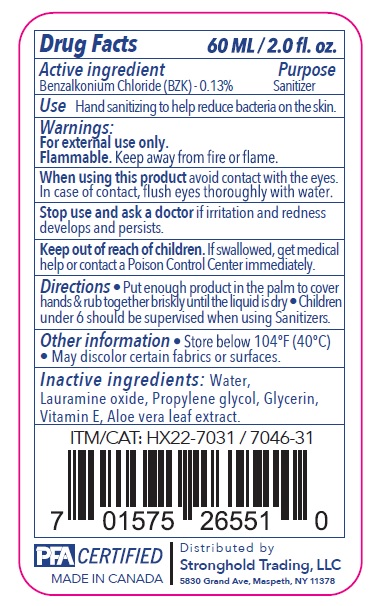 DRUG LABEL: Hand Sanitizer Alcohol Free
NDC: 50157-050 | Form: SOLUTION
Manufacturer: Brands International Corp
Category: otc | Type: HUMAN OTC DRUG LABEL
Date: 20211129

ACTIVE INGREDIENTS: BENZALKONIUM CHLORIDE 0.13 g/100 mL
INACTIVE INGREDIENTS: .ALPHA.-TOCOPHEROL ACETATE; WATER; PROPYLENE GLYCOL; GLYCERIN; ALOE VERA LEAF; LAURAMINE OXIDE

NYC HEALTH+ HOSPITALS HAND SANITIZER

ACTIVE INGREDIENT

Benzalkonium Chloride 0.13% -----Sanitizer

Use

As a sanitizer to help reduce bacteria on the skin

Directions

Put enough product in the palm to cover hands and rub together briskly until the liquid is dry. Children under 6 should be supervised using sanitizer

Warnings

FOR EXTERNALUSE ONLY. avoid contact with eyes. In case of contact with eyes, flush your eyes thoroughly with water. consult your doctor. Discontinue use if skin irritation or redness develops

General Warning

Keep out of reach of children. if swallowed, get medical help or contact poison control center immidiately

Inactive Ingredients

Water, Lauramine oxide, propylene glycol, glycerin, vitamin e, aloe vera leaf extract

Purpose

Sanitizer